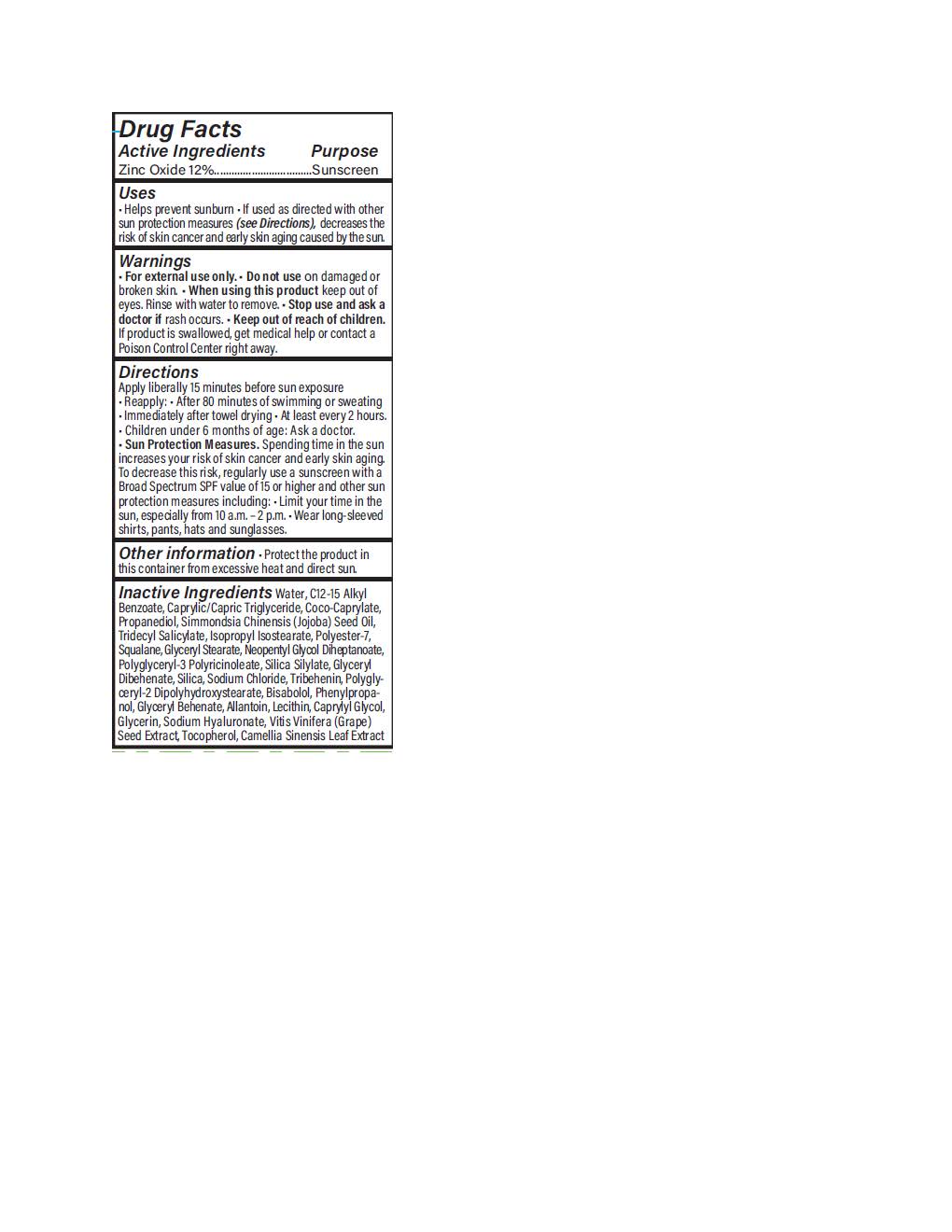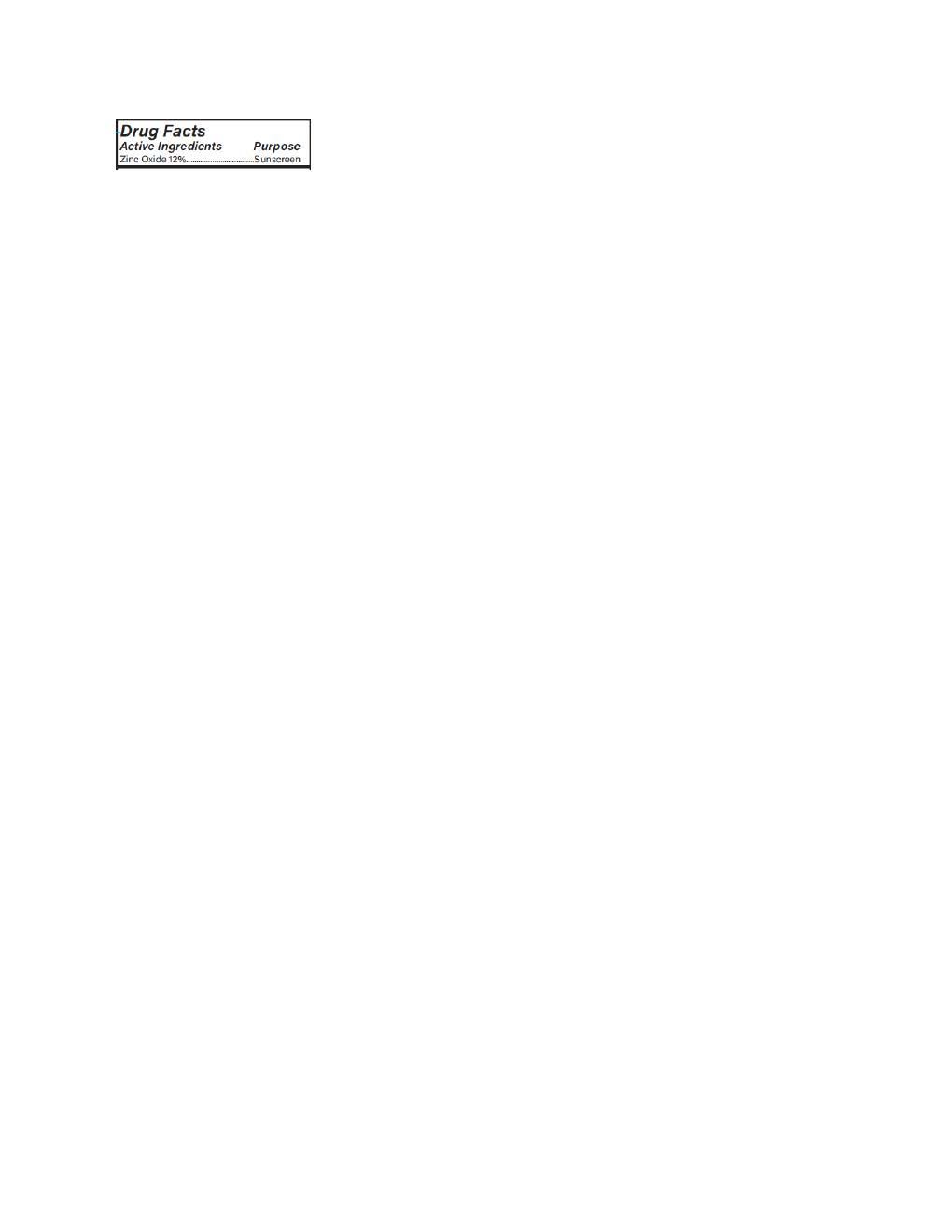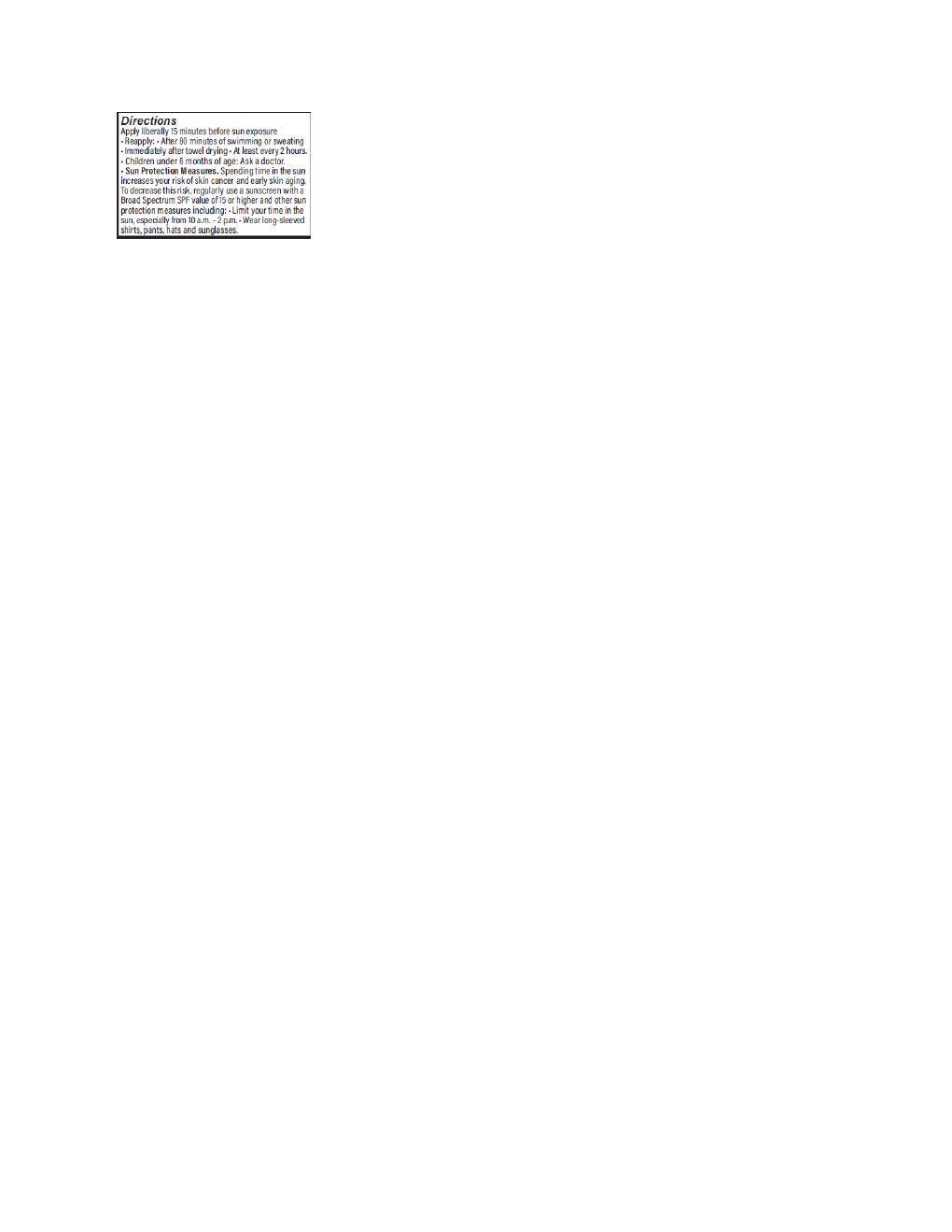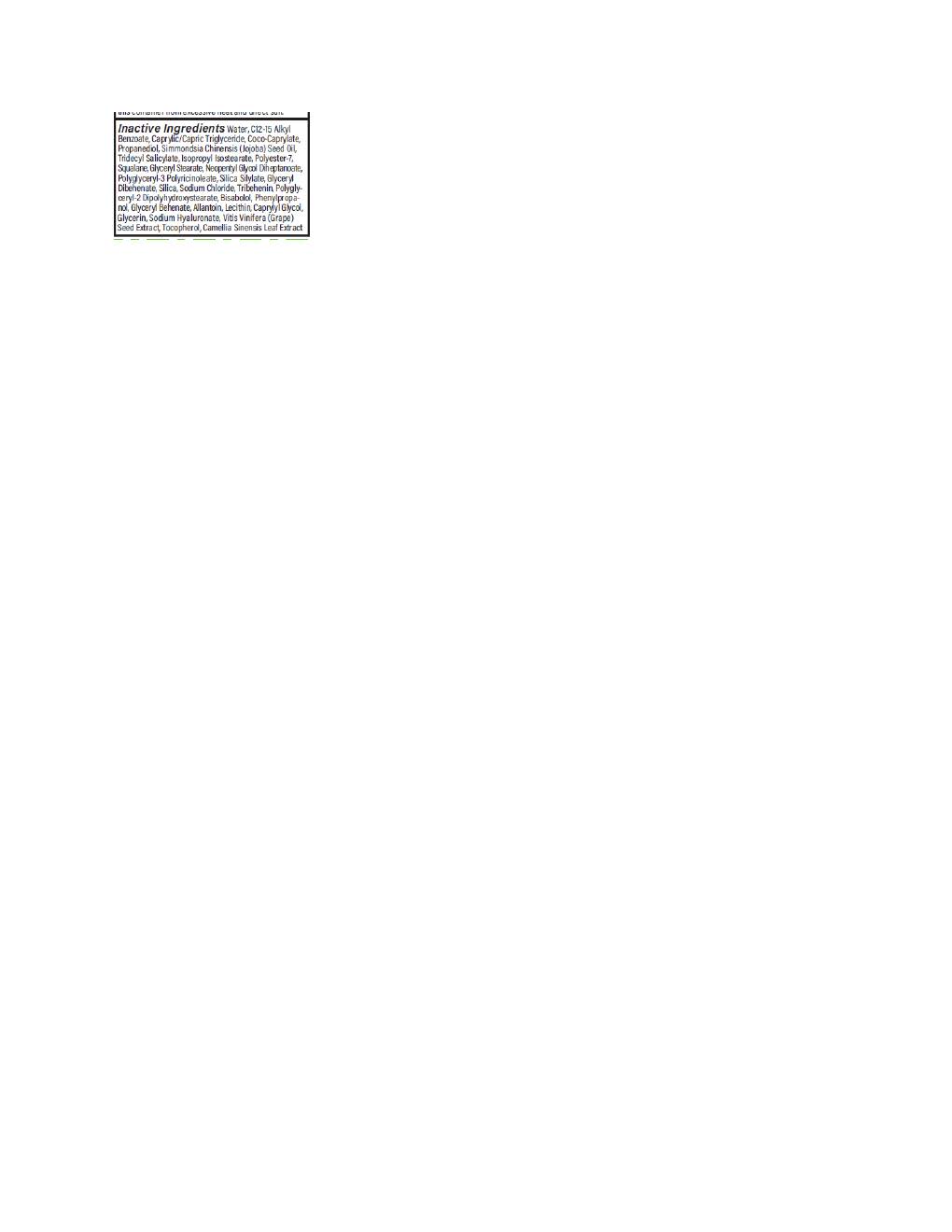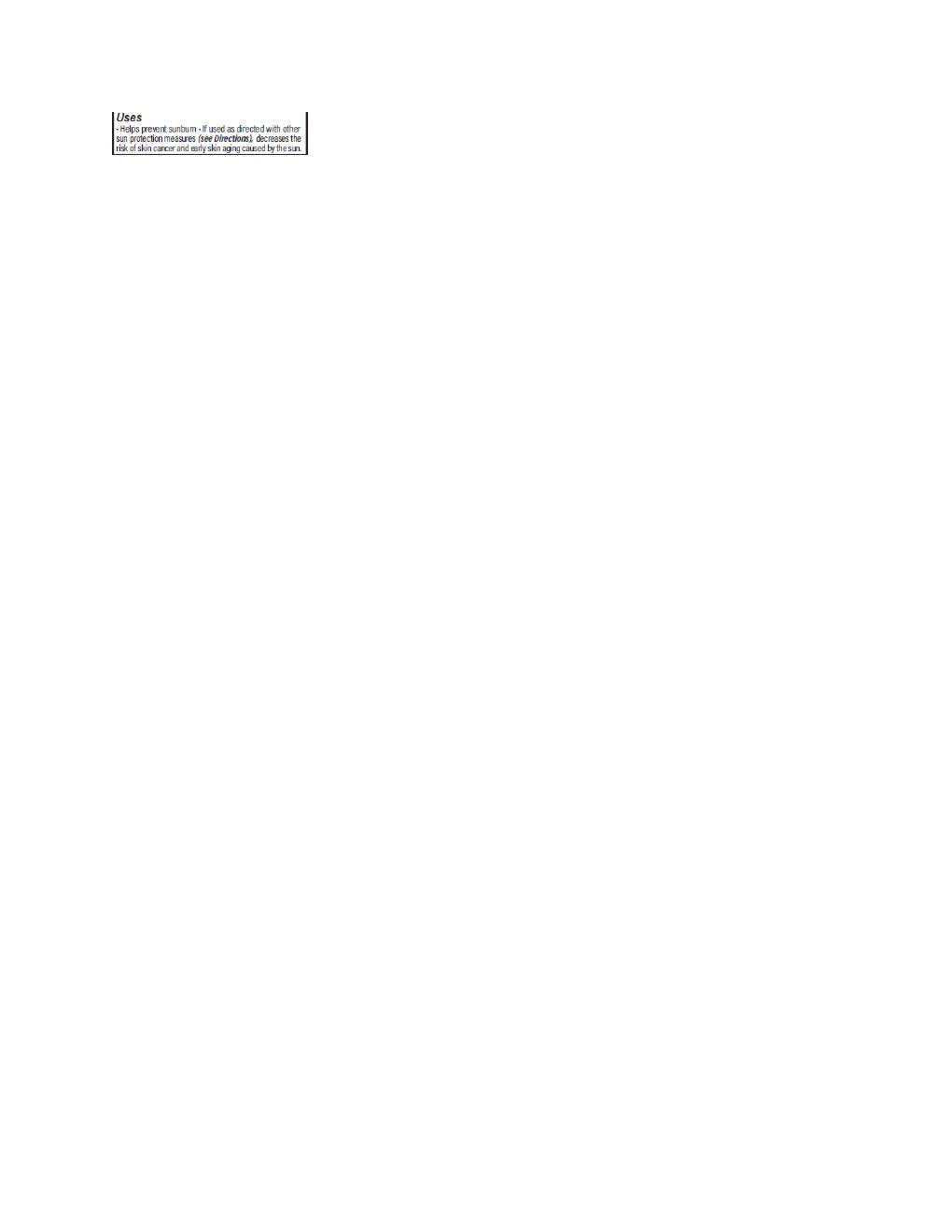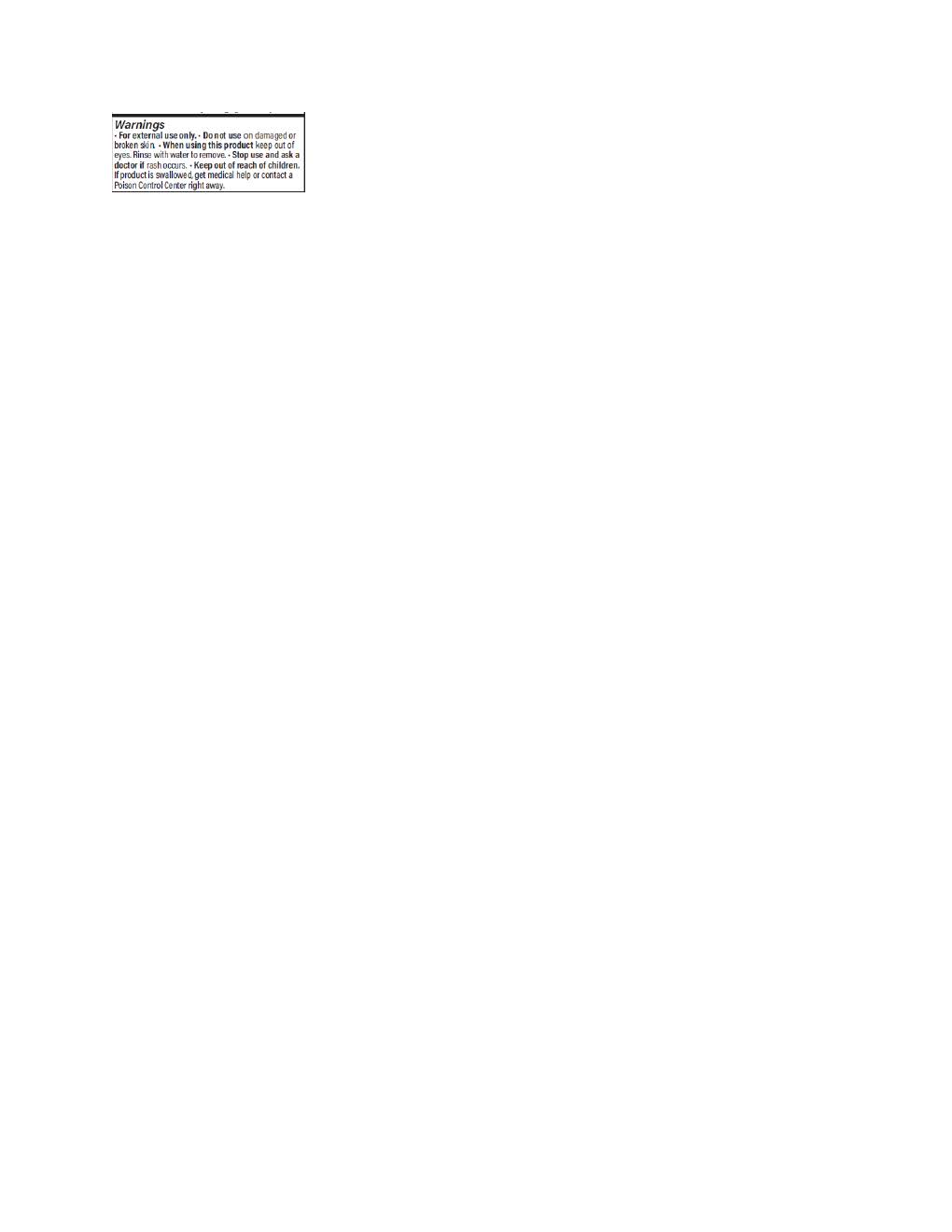 DRUG LABEL: Aspen Islanders Sheer Mineral Sport
NDC: 83382-1005 | Form: LOTION
Manufacturer: Aspen Islanders LLC
Category: otc | Type: HUMAN OTC DRUG LABEL
Date: 20251114

ACTIVE INGREDIENTS: ZINC OXIDE 132 mg/1 mL
INACTIVE INGREDIENTS: COCO-CAPRYLATE; ISOPROPYL ISOSTEARATE; GLYCERYL DIBEHENATE; WATER; POLYESTER-7; LECITHIN, SOYBEAN; TOCOPHEROL; ALKYL (C12-15) BENZOATE; VITIS VINIFERA SEED; NEOPENTYL GLYCOL DIHEPTANOATE; SILICON DIOXIDE; TRIDECYL SALICYLATE; SIMMONDSIA CHINENSIS SEED; PROPANEDIOL; .ALPHA.-BISABOLOL, (+)-; PHENYLPROPANOL; SQUALANE; POLYGLYCERYL-2 DIPOLYHYDROXYSTEARATE; ALLANTOIN; SODIUM CHLORIDE; TRIBEHENIN; CAPRYLYL GLYCOL; GLYCERIN

Aspen Islanders Sheer Mineral Sport